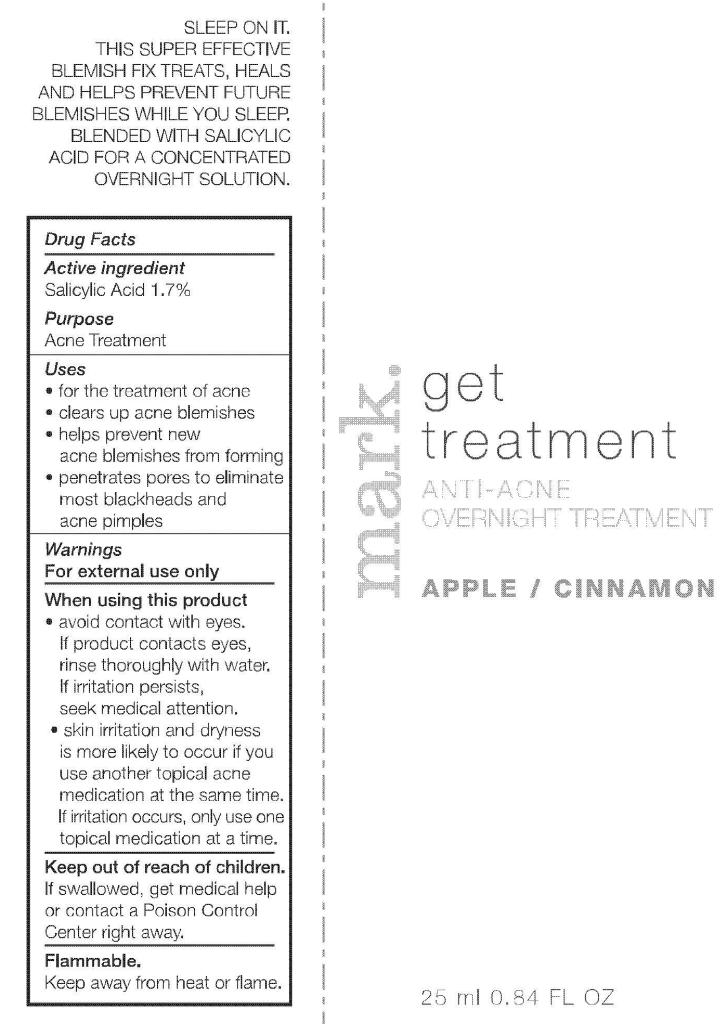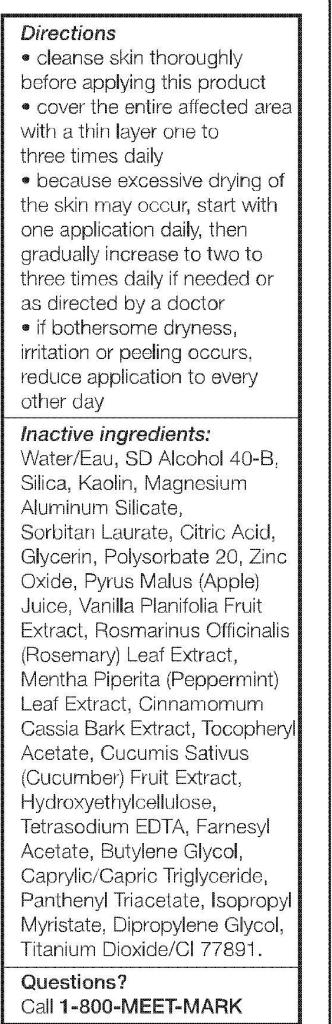 DRUG LABEL: mark.
NDC: 10096-0234 | Form: GEL
Manufacturer: Avon Products, Inc.
Category: otc | Type: HUMAN OTC DRUG LABEL
Date: 20101216

ACTIVE INGREDIENTS: SALICYLIC ACID	 0.425 mL/25 mL
INACTIVE INGREDIENTS: WATER	; MAGNESIUM ALUMINUM SILICATE	; GLYCERIN	; POLYSORBATE 20	; ZINC OXIDE	; TITANIUM DIOXIDE	

Drug Facts

Active Ingredient

Salicylic Acid 1.7%

Purpose

Acne Treatment

Uses

- for the treatment of acne
- clears up acne blemishes
- helps prevent new acne blemishes from forming
- penetrates pores to eliminate most blackheads and acne pimples

Warnings
For external use only

When using this product

- avoid contact with eyes. If product contacts eyes, rinse thoroughly with water. If irritation persists seek medical attention.
- skin irritation and dryness is more likely to occur if you use another topical acne medication at the same time. If irritation occurs, only use one topical medication at a time.

Keep out of reach of children.

If swallowed, get medical help or contact a Poison Control Center right away.

STORAGE AND HANDLING

Flammable.

Keep away from heat or flame.

Directions

- cleanse skin thoroughly before applying this product
- cover the entire affected area with a thin layer one to three times daily
- because excessive drying of the skin may occur, start with one application daily, then gradually increase to two to three times daily if needed of as directed by a doctor
- if bothersome dryness, irritation of peeling occurs, reduce application to every other day

Inactive Ingredients:

WATER/EAU
SD ALCOHOL 40-B
SILICA
KAOLIN
MAGNESIUM ALUMINUM SILICATE
SORBITAN LAURATE
CITRIC ACID
GLYCERIN
POLYSORBATE 20
ZINC OXIDE
PYRUS MALUS (APPLE) JUICE
VANILLA PLANIFOLIA FRUIT EXTRACT
ROSMARINUS OFFICINALIS (ROSEMARY) LEAF EXTRACT
MENTHA PIPERITA (PEPPERMINT) LEAF EXTRACT
CINNAMOMUM CASSIA BARK EXTRACT
TOCOPHERYL ACETATE
CUCUMIS SATIVUS (CUCUMBER) FRUIT EXTRACT
HYDROXYETHYLCELLULOSE
TETRASODIUM EDTA
FARNESYL ACETATE
BUTYLENE GLYCOL
CAPRYLIC/CAPRIC TRIGLYCERIDE
PANTHENYL TRIACETATE
ISOPROPYL MYRISTATE
DIPROPYLENE GLYCOL
TITANIUM DIOXIDE/CI 77891

Questions?

Call 1-800-MEET-MARK